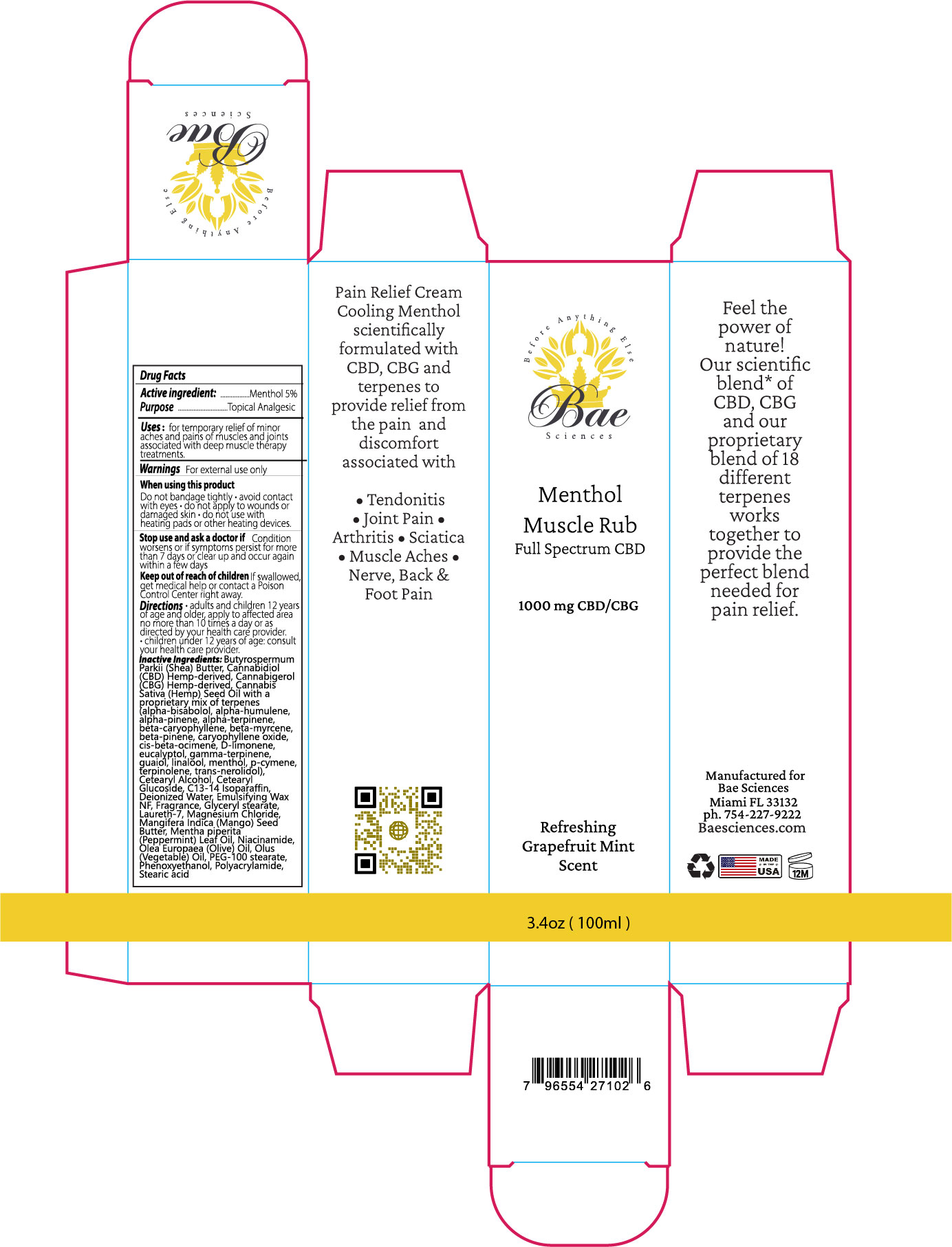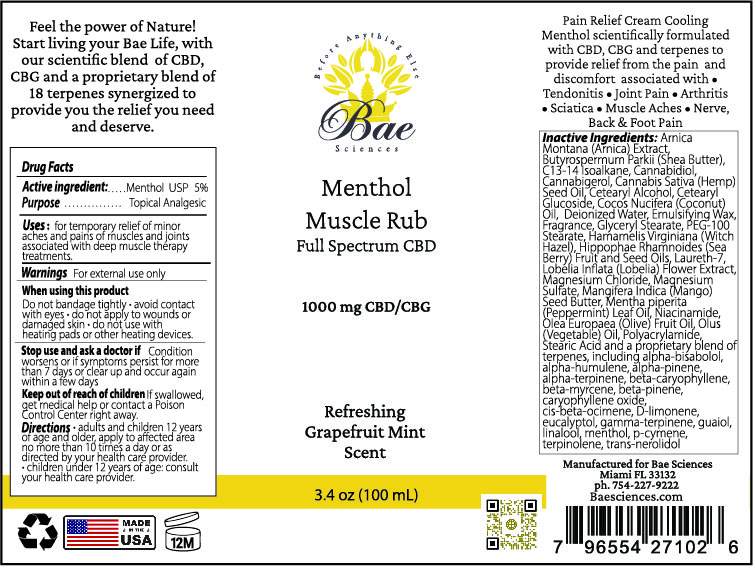 DRUG LABEL: Bae Sciences Menthol Muscle Rub
NDC: 76348-505 | Form: LOTION
Manufacturer: Renu Laboratories, Inc.
Category: otc | Type: HUMAN OTC DRUG LABEL
Date: 20230818

ACTIVE INGREDIENTS: MENTHOL 5 g/95 g
INACTIVE INGREDIENTS: PEPPERMINT OIL; NEROLIDOL; MYRCENE; LINALOOL, (+/-)-; .BETA.-CARYOPHYLLENE OXIDE; LIMONENE, (+)-; P-CYMENE; CANNABIDIOL; STEARIC ACID; OLIVE OIL; CETEARYL GLUCOSIDE; C13-14 ISOPARAFFIN; CETOSTEARYL ALCOHOL; LOBELIA INFLATA LEAF; MANGIFERA INDICA SEED BUTTER; CARYOPHYLLENE; .BETA.-PINENE; EUCALYPTOL; .GAMMA.-TERPINENE; SHEA BUTTER; CANNABIGEROL; WATER; MAGNESIUM SULFATE, UNSPECIFIED; CANNABIS SATIVA SEED OIL; COCONUT OIL; .ALPHA.-BISABOLOL, (+/-)-; HUMULENE; .ALPHA.-PINENE; HIPPOPHAE RHAMNOIDES FRUIT OIL; MAGNESIUM CHLORIDE; CORN OIL; POLYACRYLAMIDE (10000 MW); .BETA.-OCIMENE, (3Z)-; TERPINOLENE; WHITE WAX; GLYCERYL MONOSTEARATE; PEG-100 STEARATE; HIPPOPHAE RHAMNOIDES SEED OIL; WITCH HAZEL; LAURETH-7; ARNICA MONTANA; NIACINAMIDE; GUAIOL

BAE SCIENCES MENTHOL MUSCLE RUB

ACTIVE INGREDIENT

Menthol USP 5%

PURPOSE

Topical Analgesic

INDICATIONS AND USAGE

Uses: for temporary relief of minor aches and pains of muscles and joints associated with deep-muscle therapy treatments.

WARNINGS

For external use only

When using this product:

Do not bandage tightly

- avoid contact with eyes
- do not apply to wounds or damaged skin
- do not use with heating pads or other heating devices.

Stop use and ask a doctor if

Condition worsens or if symptoms persist for more than 7 days or

clear up and occur again within a few days

Keep out of reach of children

If swallowed, get medical help or contact a Poison Control Center right away.

Directions

- adults and children 12 years of age and older, apply to affected area no more than 10 times a day or as directed by your health care provider.
- children under 12 years of age, consult your health care provider.

STATEMENT OF IDENTITY

Bae Sciences Menthol Muscle Rub

QUESTIONS

Manufactured for Bae Sciences

Miami, FL 33132

ph. 754-227-9222

Baesciences.com

INACTIVE INGREDIENT

Arnica Montana (Arnica) Extract, Butyrospermum Parkii (Shea) Butter, C13-14 Isoalkane, Cannabidiol, Cannabigerol, Cannabis Sativa (Hemp) Seed Oil, Deionized Water, Emulsifying Wax, Fragrance, Glyceryl Stearate, PEG-100 Stearate, Hamamelis Virginiana (Witch Hazel), Hippophae Rhamnoides (Sea Berry) Fruit and Seed Oils, Laureth-7, Lobelia Inflata (Lobelia) Flower Extract, Magnesium Chloride, Magnesium Sulfate, Mangifera Indica (Mango) Seed Butter, Mentha piperita (Peppermint) Oil, Niacinamide, Olea Europaea (Olive) Fruit Oil, Olus (Vegetable) Oil, Polyacrylamide, Stearic Acid and a proprietary blend of terpenes, including alpha-bisabolol, alpha-humulene, alpha-pinene, alpha-terpinene, beta-caryophyllene, beta-myrcene, beta-pinene, caryophyllene oxide, cis-beta-ocimene, D-limonene, eucalyptol, gamma-terpinene, guaiol, linalool, menthol, p-cymene, terpinolene, trans-nerolidiol

PRODUCT LABEL ART AND PRODUCT BOX ART